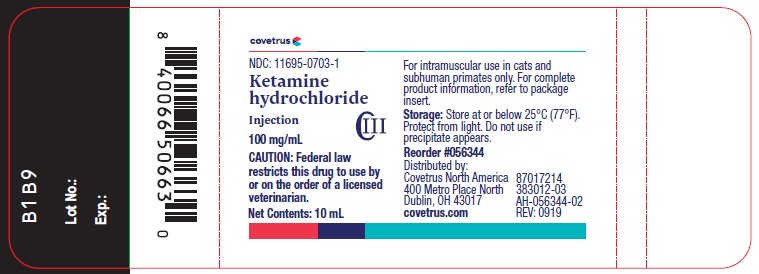 DRUG LABEL: Ketamine hydrochloride
NDC: 11695-0703 | Form: INJECTION
Manufacturer: Covetrus North America
Category: animal | Type: PRESCRIPTION ANIMAL DRUG LABEL
Date: 20250501
DEA Schedule: CIII

ACTIVE INGREDIENTS: KETAMINE HYDROCHLORIDE 100 mg/1 mL
INACTIVE INGREDIENTS: BENZETHONIUM CHLORIDE 0.1 mg/1 mL; WATER

Ketamine hydrochloride injection

Approved by FDA under NADA # 045-290

Veterinary injection

For intramuscular use in cats and subhuman primates only

Caution:

Federal law restricts this drug to use by or on the order of a licensed veterinarian.

Description:

Ketamine hydrochloride injection is a rapid-acting, nonnarcotic, nonbarbiturate agent for anesthetic use in cats and for restraint in subhuman primates. It is chemically designated dl 2-(o-chlorophenyl)-2-(methylamino) cyclohexanone hydrochloride and is supplied as a slightly acid (pH 3.5 to 5.5) solution for intramuscular injection. Each mL contains 100 mg ketamine base (equivalent to 115 mg ketamine hydrochloride) and not more than 0.1 mg benzethonium chloride as a preservative.

Indications:

Ketamine hydrochloride injection may be used in cats for restraint or as the sole anesthetic agent for diagnostic or minor, brief, surgical procedures that do not require skeletal muscle relaxation. It may be used in subhuman primates for restraint.

Dosage and administration:

Ketamine hydrochloride injection is well tolerated by cats and subhuman primates when administered by intramuscular injection.

Fasting prior to induction of anesthesia or restraint with Ketamine hydrochloride injection is not essential; however, when preparing for elective surgery, it is advisable to withhold food for at least six hours prior to administration of Ketamine hydrochloride injection.

Anesthesia may be of shorter duration in immature cats. Restraint in subhuman primate neonates (less than 24 hours of age) is difficult to achieve.

As with other anesthetic agents, the individual response to Ketamine hydrochloride injection is somewhat varied depending upon the dose, general condition and age of the subject so that dosage recommendations cannot be absolutely fixed.

Dosage – Cats:

A dose of 11 mg/kg (5 mg/lb) is recommended to produce restraint. Dosages from 22 to 33 mg/kg (10 to 15 mg/lb) produce anesthesia that is suitable for diagnostic or minor surgical procedures that do not require skeletal muscle relaxation.

Subhuman primates:

The recommended restraint dosages of Ketamine hydrochloride injection for the following species are: Cercocebus torquatus (white-collared mangabey), Papio cynocephalus (yellow baboon), Pan troglodytes verus (chimpanzee), Papio anubis (olive baboon), Pongo pygmaeus (orangutan), Macaca nemestrina (pig-tailed macaque) 5 to 7.5 mg/kg; Presbytis entellus (entellus langur) 3 to 5 mg/kg; Gorilla gorilla gorilla (gorilla) 7 to 10 mg/kg; Aotus trivirgatus (night monkey) 10 to 12 mg/kg; Macaca mulatta (rhesus monkey) 5 to 10 mg/kg; Cebus capucinus (white-throated capuchin) 13 to 15 mg/kg; and Macaca fascicularis (crab-eating macaque), Macaca radiata (bonnet macaque) and Saimiri sciureus (squirrel monkey) 12 to 15 mg/kg.

A single intramuscular injection produces restraint suitable for TB testing; radiography, physical examination or blood collection.

Contraindications:

Ketamine hydrochloride injection is contraindicated in cats and subhuman primates suffering from renal or hepatic insufficiency.

Ketamine hydrochloride injection is detoxified by the liver and excreted by the kidneys; therefore, any preexistent hepatic or renal pathology or impairment of function can be expected to result in prolonged anesthesia; related fatalities have been reported.

Precautions:

In cats, doses in excess of 50 mg/kg during any single procedure should not be used. The maximum recommended dose in subhuman primates is 40 mg/kg.

To reduce the incidence of emergence reactions, animals should not be stimulated by sound or handling during the recovery period. However, this does not preclude the monitoring of vital signs.

Apnea, respiratory arrest, cardiac arrest and death have occasionally been reported with ketamine used alone, and more frequently when used in conjunction with sedatives or other anesthetics. Close monitoring of patients is strongly advised during induction, maintenance and recovery from anesthesia.

Color of solution may vary from colorless to very slightly yellowish and may darken upon prolonged exposure to light. This darkening does not affect potency. Do not use if precipitate appears.

Adverse reactions:

Respiratory depression may occur following administration of high doses of Ketamine hydrochloride injection. If at any time respiration becomes excessively depressed and the animal becomes cyanotic, resuscitative measures should be instituted promptly. Adequate pulmonary ventilation using either oxygen or room air is recommended as a resuscitative measure.

Adverse reactions reported have included emesis, salivation, vocalization, erratic recovery and prolonged recovery, spastic jerking movements, convulsions, muscular tremors, hypertonicity, opisthotonos, dyspnea and cardiac arrest. In the cat, myoclonic jerking and/or mild tonic convulsions can be controlled by ultrashort-acting barbiturates which should be given to effect. The barbiturates should be administered intravenously at a dose level of one-sixth to one-fourth the usual dose for the product being used.

Acepromazine may also be used. However, recent information indicates that some phenothiazine derivatives may potentiate the toxic effects of organic phosphate compounds such as found in flea collars and certain anthelmintics. A study has indicated that ketamine hydrochloride alone does not potentiate the toxic effects of organic phosphate compounds.

To report suspected adverse reactions, to obtain a Safety Data Sheet or for technical assistance, call 1-855-724-3461.

For additional information about adverse drug experience reporting for animal drugs, contact FDA at 1-888-FDA-VETS, or www.fda.gov/reportanimalae.

Action:

Ketamine hydrochloride injection is a rapid-acting agent whose pharmacological action is characterized by profound analgesia, normal pharyngeal-laryngeal reflexes, mild cardiac stimulation and respiratory depression. Skeletal muscle tone is variable and may be normal, enhanced or diminished. The anesthetic state produced does not fit into the conventional classification of stages of anesthesia, but instead Ketamine hydrochloride injection produces a state of unconsciousness which has been termed “dissociative” anesthesia in that it appears to selectively interrupt association pathways to the brain before producing somesthetic sensory blockade.

In contrast to other anesthetics, protective reflexes, such as coughing and swallowing are maintained under Ketamine hydrochloride injection anesthesia. The degree of muscle tone is dependent upon level of dose; therefore, variations in body temperature may occur. At low dosage levels there may be an increase in muscle tone and a concomitant slight increase in body temperature. However, at high dosage levels there is some diminution in muscle tone and a resultant decrease in body temperature, to the point where supplemental heat may be advisable.

In cats, there is usually some transient cardiovascular stimulation, increased cardiac output with slight increase in mean systolic pressure with little or no change in total peripheral resistance. At higher doses the respiratory rate is usually decreased.

The assurance of a patent airway is greatly enhanced by virtue of maintained pharyngeal-laryngeal reflexes. Although some salivation is occasionally noted, the persistence of the swallowing reflex aids in minimizing the hazards associated with ptyalism. Salivation may be effectively controlled with atropine sulfate in dosages of 0.04 mg/kg (0.02 mg/lb) in cats and 0.01 to 0.05 mg/kg (0.005 to 0.025 mg/lb) in subhuman primates.

Other reflexes, e.g., corneal, pedal, etc., are maintained during Ketamine hydrochloride injection anesthesia, and should not be used as criteria for judging depth of anesthesia. The eyes normally remain open with the pupils dilated. It is suggested that a bland ophthalmic ointment be applied to the cornea if anesthesia is to be prolonged.

Following administration of recommended doses, cats become ataxic in about 5 minutes with anesthesia usually lasting from 30 to 45 minutes at higher doses. At the lower doses, complete recovery usually occurs in 4 to 5 hours but with higher doses recovery time is more prolonged and may be as long as 24 hours.

In studies involving 14 species of subhuman primates represented by at least 10 anesthetic episodes for each species, the median time to restraint ranged from 1.5 [Aotus trivirgatus (night monkey) and Cebus capucinus (white-throated capuchin)] to 5.3 minutes [Macaca nemestrina (pig-tailed macaque)]. The median duration of restraint ranged between 20 and 55 minutes in all but five of the species studied. Total time from injection to end of restraint ranged from 43 [Saimiri sciureus (squirrel monkey)] to 183 minutes [Macaca nemestrina (pig-tailed macaque)] after injection. Recovery is generally smooth and uneventful. The duration is dose related.

By single intramuscular injection, Ketamine hydrochloride injection usually has a wide margin of safety in cats and subhuman primates. In cats, cases of prolonged recovery and death have been reported.

Clinical studies:

Ketamine hydrochloride injection has been clinically studied in subhuman primates in addition to those species listed under Dosage and administration. Dosages for restraint in these additional species, based on limited clinical data, are: Cercopithecus aethiops (grivet), Papio papio (guinea baboon) 10 to 12 mg/kg; Erythrocebus patas patas (patas monkey) 3 to 5 mg/kg; Hylobates lar (white-handed gibbon) 5 to 10 mg/kg; Lemur catta (ringtailed lemur) 7.5 to 10 mg/kg; Macaca fuscata (Japanese macaque) 5 mg/kg; Macaca speciosa (stumptailed macaque) and Miopithecus talapoin (mangrove monkey) 5 to 7.5 mg/kg; and Symphalangus syndactylus (siamangs) 5 to 7 mg/kg.

Storage information:

Store at or below 25°C (77°F). Protect from light. When used as labeled, there is no limit on the number of punctures throughout the full expiry period.

How supplied:

Ketamine hydrochloride injection, 100 mg/mL is supplied in 10 mL vials.

NDC 11695-0703-1

10 mL vial

Distributed by:

Covetrus North America

400 Metro Place North

Dublin, OH 43017

covetrus.com

AH-Ketamine

hydrochloride inj-03

REV: 0919

383012-03

Prinicpal Display Panel – 10 mL Container Label

Covetrus

NDC 11695-0703-1

Ketamine hydrochloride injection

100 mg/mL

CAUTION: Federal law restricts this drug to use by or on the order of a licensed veterinarian.

Net Contents: 10 mL